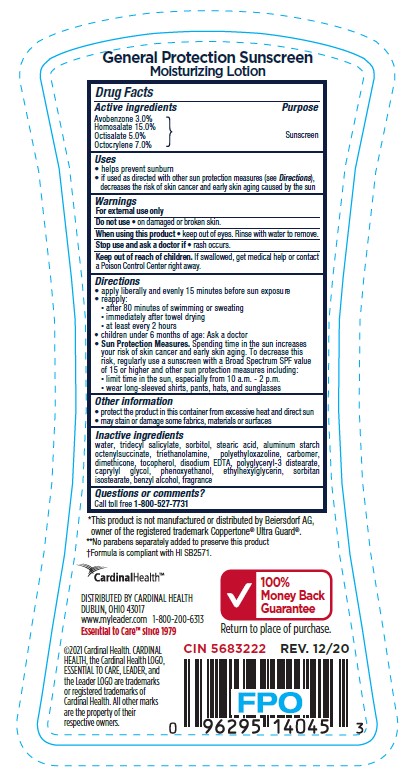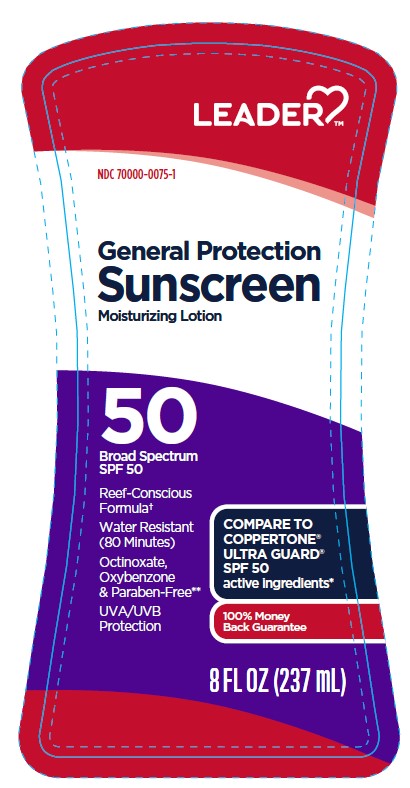 DRUG LABEL: Cardinal Health Leader General Protection Sunscreen SPF 50
NDC: 70000-0075 | Form: LOTION
Manufacturer: CARDINAL HEALTH, INC.
Category: otc | Type: HUMAN OTC DRUG LABEL
Date: 20251202

ACTIVE INGREDIENTS: AVOBENZONE 30 mg/1 g; OCTOCRYLENE 70 mg/1 g; HOMOSALATE 150 mg/1 g; OCTISALATE 50 mg/1 g
INACTIVE INGREDIENTS: WATER; CARBOMER INTERPOLYMER TYPE A (ALLYL SUCROSE CROSSLINKED); SORBITOL; TROLAMINE; POLYETHYLOXAZOLINE (5000 MW); DIMETHICONE; TRIDECYL SALICYLATE; PHENOXYETHANOL; ETHYLHEXYLGLYCERIN; EDETATE DISODIUM; STEARIC ACID; .ALPHA.-TOCOPHEROL, DL-; BENZYL ALCOHOL; ALUMINUM STARCH OCTENYLSUCCINATE; POLYGLYCERYL-3 DISTEARATE; CAPRYLYL GLYCOL; SORBITAN ISOSTEARATE

Cardinal Health Leader General Protection Sunscreen SPF 50 Lotion

Active ingredients

Avobenzone 3.0%, Homosalate 15.0%, Octisalate 5.0%, Octocrylene 7.0%

Purpose

Sunscreen

Uses

• helps prevent sunburn

• if used as directed with other sun protection measures (see Directions),

decreases the risk of skin cancer and early skin aging caused by the sun

Warnings

For external use only

Do not use

• on damaged or broken skin.

When using this product

• keep out of eyes. Rinse with water to remove

Stop use and ask a doctor if

• rash occurs.

Keep out of reach of children.

If swallowed, get medical help or contact a Poison Control Center right away.

Directions

• apply liberally and evenly 15 minutes before sun exposure

reapply:

• after 80 minutes of swimming or sweating

• immediately after towel drying

• at least every 2 hours

• children under 6 months of age: Ask a doctor

Sun Protection Measures. Spending time in the sun increases

your risk of skin cancer and early skin aging. To decrease this

risk, regularly use a sunscreen with a Broad Spectrum SPF value

of 15 or higher and other sun protection measures including:

• limit time in the sun, especially from 10 a.m. - 2 p.m.

• wear long-sleeved shirts, pants, hats, and sunglasses

Other information

• protect the product in this container from excessive heat and direct sun

• may stain or damage some fabrics, materials or surfaces

Inactive ingredients

water, tridecyl salicylate, sorbitol, stearic acid, aluminum starch octenylsuccinate, triethanolamine, polyethyloxazoline, carbomer, dimethicone, tocopherol, disodium EDTA, polyglyceryl-3 distearate, caprylyl glycol, phenoxyethanol, ethylhexylglycerin, sorbitan isostearate, benzyl alcohol, fragrance

Label

Cardinal Health Leader General Protection Sunscreen SPF 50 Lotion

8 fl oz (237 mL)

NDC 70000-0075-1